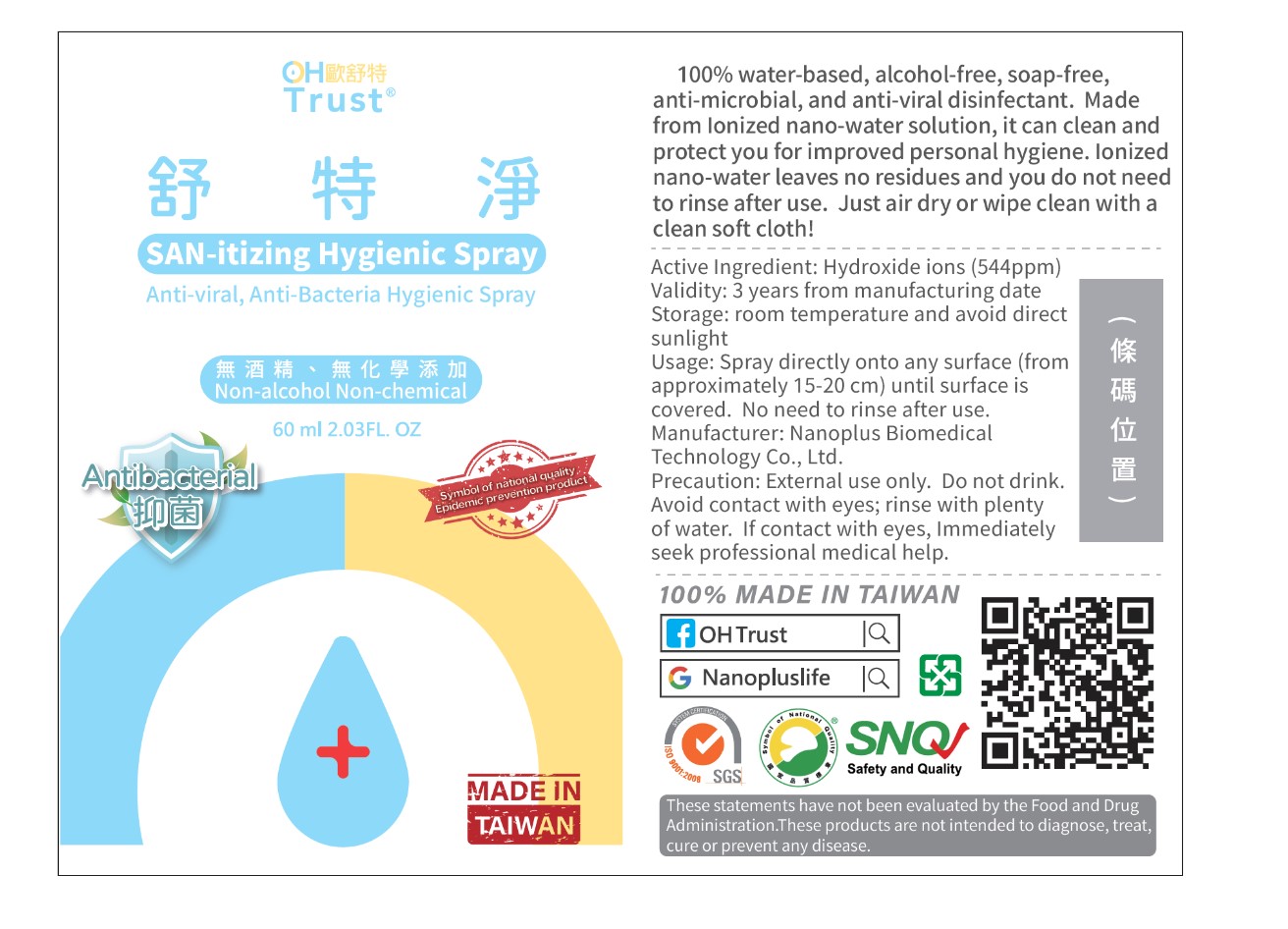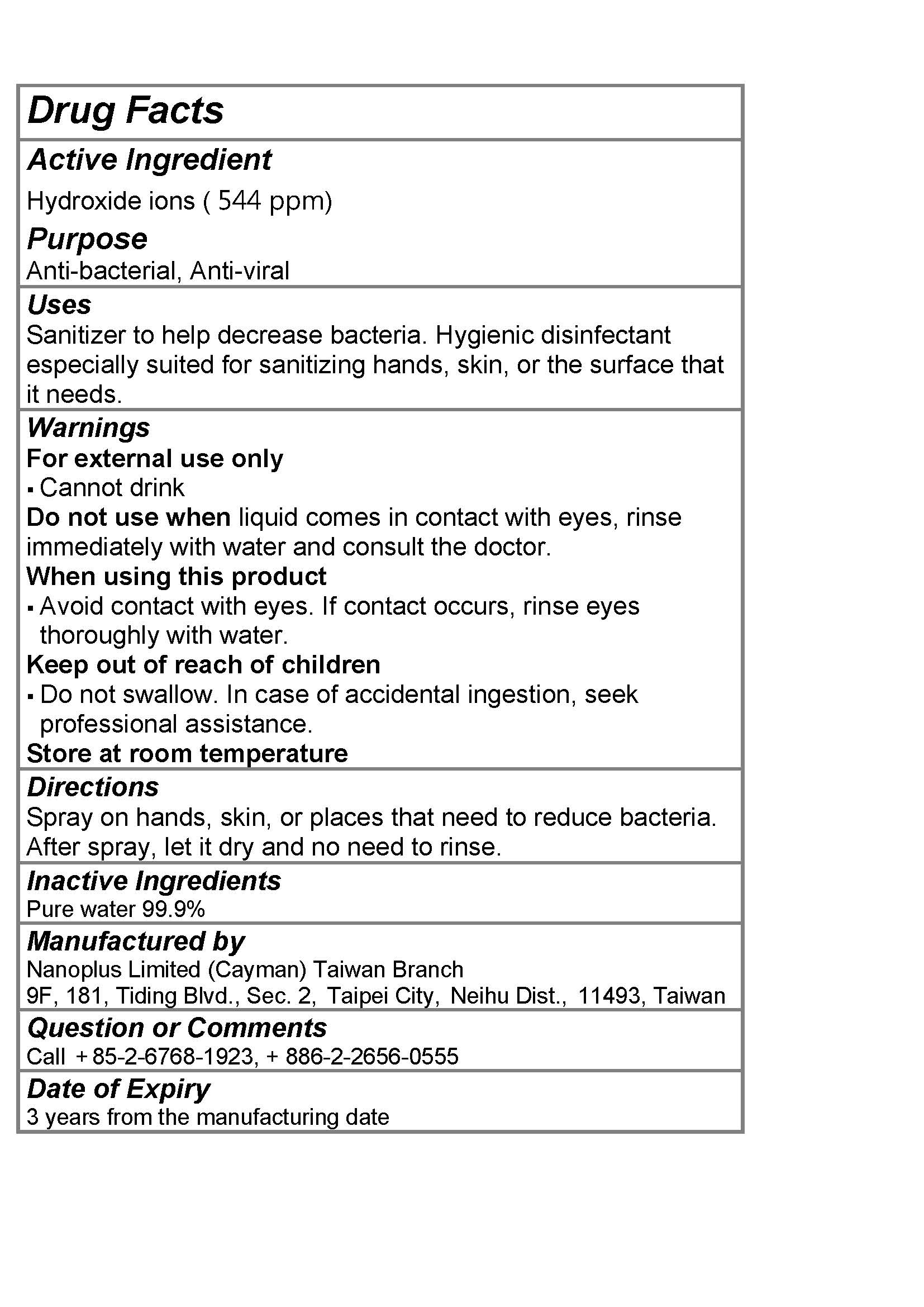 DRUG LABEL: OHTrust Nano Ion Water
NDC: 78218-007 | Form: LIQUID
Manufacturer: Kunshan Nano Environmental Protection Technology Co. Ltd.
Category: otc | Type: HUMAN OTC DRUG LABEL
Date: 20220113

ACTIVE INGREDIENTS: HYDROXIDE ION 0.0544 mg/100 mg
INACTIVE INGREDIENTS: WATER

Kunshan 007-01

Active Ingredient(s)

Hydroxide Ions (544 ppm) Purpose: Antimicrobial

Purpose

Purpose: Antimicrobial

Use

Sanitizer to help decrease bacteria. Hygienic disinfectant especially suited for sanitizing hands, skin or the surface that it needs.

Warnings

For external use only. Cannot drink

Keep out of reach of children

Do not swallow. In case of accidental ingestion, seek professional assistance.

Do not use when liquid comes in contact with eyes, rinse immediately with water and consult the doctor

When using this product avoid contact with eyes. If contact occurs, rinse eyes thoroughly with water

Keep out of reach of children

Do not swallow. In case of accidental ingestion, seek professional assistance.

Directions

Spray on hands, skin, or places that need to reduce bacteria. After spray, let it dry and no need to rinse.

Other information

Store at room temperature

Inactive ingredients

Pure Water 99.9%

Package Label - Principal Display Panel

60000 mg NDC: 78218-007-01